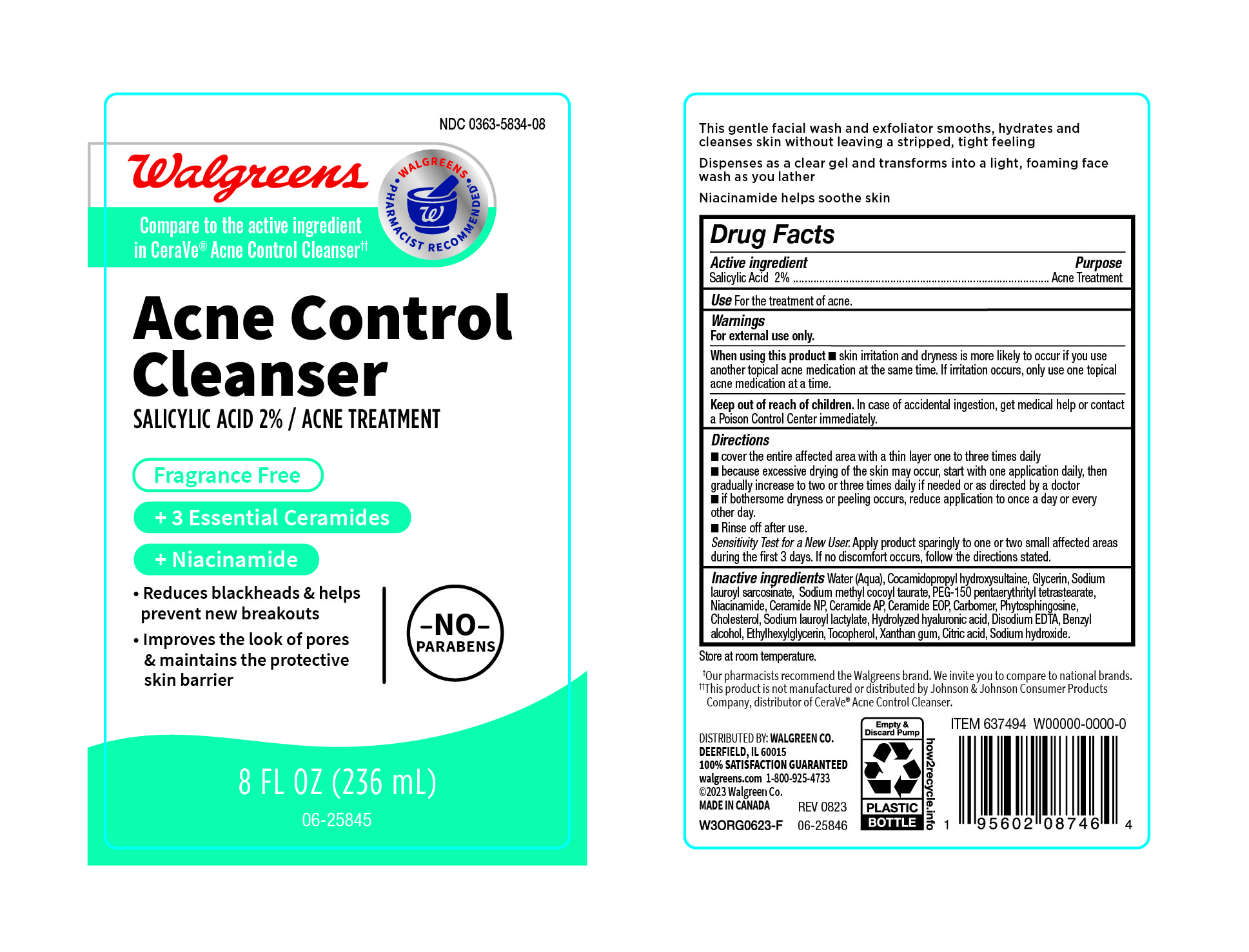 DRUG LABEL: Acne Control
NDC: 0363-5834 | Form: CREAM
Manufacturer: Walgreen
Category: otc | Type: HUMAN OTC DRUG LABEL
Date: 20241010

ACTIVE INGREDIENTS: SALICYLIC ACID 2000 mg/100 mL
INACTIVE INGREDIENTS: CARBOMER 940; ETHYLHEXYLGLYCERIN; PHYTOSPHINGOSINE; TOCOPHEROL; ANHYDROUS CITRIC ACID; SODIUM LAUROYL SARCOSINATE; PEG-150 PENTAERYTHRITYL TETRASTEARATE; CERAMIDE AP; CHOLESTEROL; SODIUM METHYL COCOYL TAURATE; NIACINAMIDE; SODIUM LAUROYL LACTYLATE; CERAMIDE 1; HYALURONIC ACID; EDETATE DISODIUM; BENZYL ALCOHOL; SODIUM HYDROXIDE; XANTHAN GUM; COCAMIDOPROPYL HYDROXYSULTAINE; CERAMIDE NP; WATER; GLYCERIN

Acne Control Cleanser

Active Ingredient

Salicylic Acid 2%

Purpose

Acne Treatment

Uses

For the treatment of acne.

Warnings

For external use only.

When using this product

- Skin irritation and drynessis more likely to occur if you use another topical acne medication at the same time. If irritation occurs, only use one topical acne medication at a time.

Keep out of reach of children

In case of accidental ingestion, get medical help or contact a Poison Control Center immediately.

Directions

- Cover the entire affected area with a thin layer one to three times daily.
- because excessive drying of the skin may occur, start with one application daily, then gradually increase to two or three times daily if needed or as directed by a doctor.
- If bothersome dryness or peeling occurs, reduce application to once a day or every other day.
- Rinse off after use.

Sensitivity Test for a New user. Apply product sparingly to one or two small affected areas during the first 3 days. If no discomfort occurs, follow the directions stated.

Inactive Ingredients

Water (Aqua), Cocamidopropyl hydroxysultaine, Glycerin, Sodiumj Lauroyl sarcosinate, Sodium Methyl Cocvoyl Taurate, PEG-150 Pentaerythrityl Tetrastearate, Niacinamide, Ceramide NP, Ceramide AP, Ceramide EOP, Carbomer, Phytosphingosine, Cholesterol, Sodium Lauroyl Lactylate, Hydrolyzed Hyaluronic Acid, Disodium EDTA, Benzyl alcohol, Ethylhexylglycerin, Tocopherol, Xanthan gum, Citric Acid, Sodium Hydroxide.